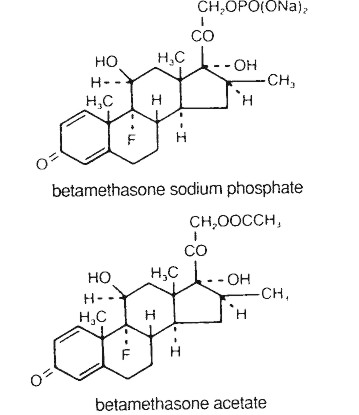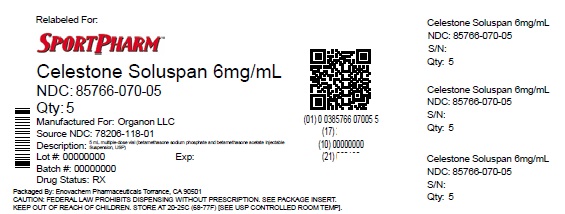 DRUG LABEL: CELESTONE SOLUSPAN
NDC: 85766-070 | Form: INJECTION, SUSPENSION
Manufacturer: Sportpharm, Inc. dba Sportpharm
Category: prescription | Type: HUMAN PRESCRIPTION DRUG LABEL
Date: 20251001

ACTIVE INGREDIENTS: BETAMETHASONE ACETATE 3 mg/1 mL; BETAMETHASONE SODIUM PHOSPHATE 3 mg/1 mL
INACTIVE INGREDIENTS: SODIUM PHOSPHATE, DIBASIC, DIHYDRATE 8.9 mg/1 mL; SODIUM PHOSPHATE, MONOBASIC, DIHYDRATE 3.8 mg/1 mL; EDETATE DISODIUM 0.1 mg/1 mL; BENZALKONIUM CHLORIDE 0.2 mg/1 mL

CELESTONE®SOLUSPAN®

(betamethasone sodium phosphate
and betamethasone acetate) Injectable Suspension, USP
30 mg/5 mL (6 mg/mL)

DESCRIPTION

CELESTONE®SOLUSPAN®Injectable Suspension is a sterile aqueous suspension containing 3 mg per milliliter betamethasone (equivalent to 3.95 mg betamethasone sodium phosphate USP) and 3 mg per milliliter betamethasone acetate. Inactive ingredients per mL: 8.9 mg dibasic sodium phosphate dihydrate; 3.8 mg monobasic sodium phosphate dihydrate; 0.1 mg edetate disodium; and 0.2 mg benzalkonium chloride as preservative. The pH is between 6.8 and 7.2.

The formula for betamethasone sodium phosphate is C22H28FNa2O8P and it has a molecular weight of 516.40. Chemically, it is 9-Fluoro-11β,17,21-trihydroxy-16β-methylpregna-1,4-diene-3,20-dione 21-(disodium phosphate).

The formula for betamethasone acetate is C24H31FO6and it has a molecular weight of 434.50. Chemically, it is 9-Fluoro-11β,17,21-trihydroxy-16β-methylpregna-1,4-diene-3,20-dione 21-acetate.

The chemical structures for betamethasone sodium phosphate and betamethasone acetate are as follows:

Betamethasone sodium phosphate is a white to practically white, odorless powder, and is hygroscopic. It is freely soluble in water and in methanol, but is practically insoluble in acetone and in chloroform.

Betamethasone acetate is a white to creamy white, odorless powder that sinters and resolidifies at about 165°C, and remelts at about 200°C-220°C with decomposition. It is practically insoluble in water, but freely soluble in acetone, and is soluble in alcohol and in chloroform.

CLINICAL PHARMACOLOGY

Glucocorticoids, naturally occurring and synthetic, are adrenocortical steroids that are readily absorbed from the gastrointestinal tract.

Naturally occurring glucocorticoids (hydrocortisone and cortisone), which also have salt-retaining properties, are used as replacement therapy in adrenocortical deficiency states. Their synthetic analogs are primarily used for their anti-inflammatory effects in disorders of many organ systems. A derivative of prednisolone, betamethasone has a 16β-methyl group that enhances the anti-inflammatory action of the molecule and reduces the sodium- and water-retaining properties of the fluorine atom bound at carbon 9.

Betamethasone sodium phosphate, a soluble ester, provides prompt activity, while betamethasone acetate is only slightly soluble and affords sustained activity.

INDICATIONS AND USAGE

When oral therapy is not feasible, the intramuscular useof CELESTONE®SOLUSPAN®Injectable Suspension is indicated as follows:

Allergic States

Control of severe or incapacitating allergic conditions intractable to adequate trials of conventional treatment in asthma, atopic dermatitis, contact dermatitis, drug hypersensitivity reactions, perennial or seasonal allergic rhinitis, serum sickness, transfusion reactions.

Dermatologic Diseases

Bullous dermatitis herpetiformis, exfoliative erythroderma, mycosis fungoides, pemphigus, severe erythema multiforme (Stevens-Johnson syndrome).

Endocrine Disorders

Congenital adrenal hyperplasia, hypercalcemia associated with cancer, nonsuppurative thyroiditis.

Hydrocortisone or cortisone is the drug of choice in primary or secondary adrenocortical insufficiency. Synthetic analogs may be used in conjunction with mineralocorticoids where applicable; in infancy mineralocorticoid supplementation is of particular importance.

Gastrointestinal Diseases

To tide the patient over a critical period of the disease in regional enteritis and ulcerative colitis.

Hematologic Disorders

Acquired (autoimmune) hemolytic anemia, Diamond-Blackfan anemia, pure red cell aplasia, selected cases of secondary thrombocytopenia.

Miscellaneous

Trichinosis with neurologic or myocardial involvement, tuberculous meningitis with subarachnoid block or impending block when used with appropriate antituberculous chemotherapy.

Neoplastic Diseases

For palliative management of leukemias and lymphomas.

Nervous System

Acute exacerbations of multiple sclerosis; cerebral edema associated with primary or metastatic brain tumor or craniotomy.

Ophthalmic Diseases

Sympathetic ophthalmia, temporal arteritis, uveitis and ocular inflammatory conditions unresponsive to topical corticosteroids.

Renal Diseases

To induce diuresis or remission of proteinuria in idiopathic nephrotic syndrome or that due to lupus erythematosus.

Respiratory Diseases

Berylliosis, fulminating or disseminated pulmonary tuberculosis when used concurrently with appropriate antituberculous chemotherapy, idiopathic eosinophilic pneumonias, symptomatic sarcoidosis.

Rheumatic DisordersAs adjunctive therapy for short-term administration (to tide the patient over an acute episode or exacerbation) in acute gouty arthritis; acute rheumatic carditis; ankylosing spondylitis; psoriatic arthritis; rheumatoid arthritis, including juvenile rheumatoid arthritis (selected cases may require low-dose maintenance therapy). For the treatment of dermatomyositis, polymyositis, and systemic lupus erythematosus.

The intra-articular or soft tissue administrationof CELESTONE SOLUSPAN Injectable Suspension is indicated as adjunctive therapy for short-term administration (to tide the patient over an acute episode or exacerbation) in acute gouty arthritis, acute and subacute bursitis, acute nonspecific tenosynovitis, epicondylitis, rheumatoid arthritis, synovitis of osteoarthritis.

The intralesional administrationof CELESTONE SOLUSPAN Injectable Suspension is indicated for alopecia areata; discoid lupus erythematosus; keloids; localized hypertrophic, infiltrated, inflammatory lesions of granuloma annulare, lichen planus, lichen simplex chronicus (neurodermatitis), and psoriatic plaques; necrobiosis lipoidica diabeticorum.

CELESTONE SOLUSPAN Injectable Suspension may also be useful in cystic tumors of an aponeurosis or tendon (ganglia).

CONTRAINDICATIONS

CELESTONE®SOLUSPAN®Injectable Suspension is contraindicated in patients who are hypersensitive to any components of this product (see DESCRIPTION).

Intramuscular corticosteroid preparations are contraindicated for idiopathic thrombocytopenic purpura.

WARNINGS

CELESTONE®SOLUSPAN®Injectable Suspension should not be administered intravenously.

Serious Neurologic Adverse Reactions with Epidural Administration

Serious neurologic events, some resulting in death, have been reported with epidural injection of corticosteroids. Specific events reported include, but are not limited to, spinal cord infarction, paraplegia, quadriplegia, cortical blindness, and stroke. These serious neurologic events have been reported with and without use of fluoroscopy. The safety and effectiveness of epidural administration of corticosteroids have not been established, and corticosteroids are not approved for this use.

General

Rare instances of anaphylactoid/anaphylactic reactions with a possibility of shock have occurred in patients receiving parenteral corticosteroid therapy (see ADVERSE REACTIONS). Use caution in patients who have a history of allergic reactions to corticosteroids.

In patients on corticosteroid therapy subjected to any unusual stress, hydrocortisone or cortisone is the drug of choice as a supplement during and after the event.

Cardio-renal

Average and large doses of corticosteroids can cause elevation of blood pressure, salt and water retention, and increased excretion of potassium. These effects are less likely to occur with the synthetic derivatives except when used in large doses. Dietary salt restriction and potassium supplementation may be necessary. All corticosteroids increase calcium excretion.

Literature reports suggest an apparent association between use of corticosteroids and left ventricular free wall rupture after a recent myocardial infarction; therefore, therapy with corticosteroids should be used with great caution in these patients.

There have been cases reported in which concomitant use of amphotericin B and hydrocortisone was followed by cardiac enlargement and congestive heart failure (see PRECAUTIONS, Drug Interactions, Amphotericin B Injection and Potassium-Depleting Agentssection).

Endocrine

Corticosteroids can produce reversible hypothalamic pituitary adrenal (HPA) axis suppression with the potential for glucocorticosteroid insufficiency after withdrawal of treatment.

Metabolic clearance of corticosteroids is decreased in hypothyroid patients and increased in hyperthyroid patients. Changes in thyroid status of the patient may necessitate adjustment in dosage.

Pheochromocytoma crisis, which may be fatal, has been reported after administration of systemic corticosteroids, including betamethasone. In patients with suspected or identified pheochromocytoma, consider the risk of pheochromocytoma crisis prior to administering corticosteroids.

Immunosuppression and Increased Risk of Infection

Corticosteroids, including CELESTONE SOLUSPAN, suppress the immune system and increase the risk of infection with any pathogen, including viral, bacterial, fungal, protozoan, or helminthic pathogens. Corticosteroids can:

- Reduce resistance to new infections
- Exacerbate existing infections
- Increase the risk of disseminated infections
- Increase the risk of reactivation or exacerbation of latent infections
- Mask some signs of infection

Corticosteroid-associated infections can be mild but can be severe and at times fatal. The rate of infectious complications increases with increasing corticosteroid dosages.

Monitor for the development of infection and consider CELESTONE SOLUSPAN withdrawal or dosage reduction as needed.

Do not administer CELESTONE SOLUSPAN by an intraarticular, intrabursal, intratendinous or intralesional route in the presence of acute local infection.

Tuberculosis

If CELESTONE SOLUSPAN is used to treat a condition in patients with latent tuberculosis or tuberculin reactivity, reactivation of the disease may occur. During prolonged CELESTONE SOLUSPAN therapy, patients with latent tuberculosis or tuberculin reactivity should receive chemoprophylaxis.

Varicella Zoster and Measles Viral Infections

Varicella and measles can have a serious or even fatal course in non-immune patients taking corticosteroids, including CELESTONE SOLUSPAN. In corticosteroid-treated patients who have not had these diseases or are non-immune, particular care should be taken to avoid exposure to varicella and measles:

- If a CELESTONE SOLUSPAN-treated patient is exposed to varicella, prophylaxis with varicella zoster immune globulin (VZIG) may be indicated. If varicella develops, treatment with antiviral agents may be considered.
- If a CELESTONE SOLUSPAN-treated patient is exposed to measles, prophylaxis with immunoglobulin (IG) may be indicated.

Hepatitis B virus reactivation can occur in patients who are hepatitis B carriers treated with immunosuppressive dosages of corticosteroids, including CELESTONE SOLUSPAN. Reactivation can also occur infrequently in corticosteroid-treated patients who appear to have resolved hepatitis B infection.

Screen patients for hepatitis B infection before initiating immunosuppressive (eg, prolonged) treatment with CELESTONE SOLUSPAN. For patients who show evidence of hepatitis B infection, recommend consultation with physicians with expertise in managing hepatitis B regarding monitoring and consideration for hepatitis B antiviral therapy.

Fungal Infections

Corticosteroids, including CELESTONE SOLUSPAN, may exacerbate systemic fungal infections; therefore, avoid CELESTONE SOLUSPAN use in the presence of such infections unless CELESTONE SOLUSPAN is needed to control drug reactions. For patients on chronic CELESTONE SOLUSPAN therapy who develop systemic fungal infections, CELESTONE SOLUSPAN withdrawal or dosage reduction is recommended.

Amebiasis

Corticosteroids, including CELESTONE SOLUSPAN, may activate latent amebiasis. Therefore, it is recommended that latent amebiasis or active amebiasis be ruled out before initiating CELESTONE SOLUSPAN in patients who have spent time in the tropics or patients with unexplained diarrhea.

Strongyloides Infestation

Corticosteroids, including CELESTONE SOLUSPAN, should be used with great care in patients with known or suspected Strongyloides (threadworm) infestation. In such patients, corticosteroid-induced immunosuppression may lead to Strongyloides hyperinfection and dissemination with widespread larval migration, often accompanied by severe enterocolitis and potentially fatal gram-negative septicemia.

Cerebral Malaria

Avoid corticosteroids, including CELESTONE SOLUSPAN, in patients with cerebral malaria.

Vaccination

Administration of live or live, attenuated vaccines is contraindicated in patients receiving immunosuppressive doses of corticosteroids. Killed or inactivated vaccines may be administered. However, the response to such vaccines cannot be predicted. Immunization procedures may be undertaken in patients who are receiving corticosteroids as replacement therapy, eg, for Addison's disease.

Neurologic

Reports of severe medical events have been associated with the intrathecal route of administration (see ADVERSE REACTIONS, Gastrointestinaland Neurologic/Psychiatricsections).

Results from one multicenter, randomized, placebo-controlled study with methylprednisolone hemisuccinate, an IV corticosteroid, showed an increase in early mortality (at 2 weeks) and late mortality (at 6 months) in patients with cranial trauma who were determined not to have other clear indications for corticosteroid treatment. High doses of corticosteroids, including CELESTONE SOLUSPAN, should not be used for the treatment of traumatic brain injury.

Ophthalmic

Use of corticosteroids may produce posterior subcapsular cataracts, increased intraocular pressure, glaucoma with possible damage to the optic nerves, and may enhance the establishment of secondary ocular infections due to bacteria, fungi, or viruses. Consider referral to an ophthalmologist for patients who develop ocular symptoms or use corticosteroid-containing products for more than 6 weeks. The use of oral corticosteroids is not recommended in the treatment of optic neuritis and may lead to an increase in the risk of new episodes. Corticosteroids should not be used in active ocular herpes simplex.

Kaposi’s sarcoma has been reported to occur in patients receiving corticosteroid therapy, most often for chronic conditions. Discontinuation of corticosteroids may result in clinical improvement of Kaposi’s sarcoma.

PRECAUTIONS

General

This product, like many other steroid formulations, is sensitive to heat. Therefore, it should not be autoclaved when it is desirable to sterilize the exterior of the vial.

The lowest possible dose of corticosteroid should be used to control the condition under treatment. When reduction in dosage is possible, the reduction should be gradual.

Since complications of treatment with glucocorticoids are dependent on the size of the dose and the duration of treatment, a risk/benefit decision must be made in each individual case as to dose and duration of treatment and as to whether daily or intermittent therapy should be used.

Cardio-renal

As sodium retention with resultant edema and potassium loss may occur in patients receiving corticosteroids, these agents should be used with caution in patients with congestive heart failure, hypertension, or renal insufficiency.

Endocrine

Drug-induced secondary adrenocortical insufficiency may be minimized by gradual reduction of dosage. This type of relative insufficiency may persist for months after discontinuation of therapy. Therefore, in any situation of stress occurring during that period, naturally occurring glucocorticoids (hydrocortisone cortisone), which also have salt-retaining properties, rather than betamethasone, are the appropriate choices as replacement therapy in adrenocortical deficiency states.

Gastrointestinal

Steroids should be used with caution in active or latent peptic ulcers, diverticulitis, fresh intestinal anastomoses, and nonspecific ulcerative colitis, since they may increase the risk of a perforation.

Signs of peritoneal irritation following gastrointestinal perforation in patients receiving corticosteroids may be minimal or absent.

There is an enhanced effect of corticosteroids in patients with cirrhosis.

Intra-Articular and Soft Tissue Administration

Intra-articular injected corticosteroids may be systemically absorbed.

Appropriate examination of any joint fluid present is necessary to exclude a septic process.

A marked increase in pain accompanied by local swelling, further restriction of joint motion, fever, and malaise are suggestive of septic arthritis. If this complication occurs and the diagnosis of sepsis is confirmed, appropriate antimicrobial therapy should be instituted.

Injection of a steroid into an infected site is to be avoided. Local injection of a steroid into a previously injected joint is not usually recommended.

Corticosteroid injection into unstable joints is generally not recommended.

Intra-articular injection may result in damage to joint tissues (see ADVERSE REACTIONS, Musculoskeletalsection).

Musculoskeletal

Corticosteroids decrease bone formation and increase bone resorption both through their effect on calcium regulation (ie, decreasing absorption and increasing excretion) and inhibition of osteoblast function. This, together with a decrease in the protein matrix of the bone secondary to an increase in protein catabolism, and reduced sex hormone production, may lead to inhibition of bone growth in pediatric patients and the development of osteoporosis at any age. Special consideration should be given to patients at increased risk of osteoporosis (ie, postmenopausal women) before initiating corticosteroid therapy.

Neuro-psychiatric

Although controlled clinical trials have shown corticosteroids to be effective in speeding the resolution of acute exacerbations of multiple sclerosis, they do not show that they affect the ultimate outcome or natural history of the disease. The studies do show that relatively high doses of corticosteroids are necessary to demonstrate a significant effect (see DOSAGE AND ADMINISTRATION).

An acute myopathy has been observed with the use of high doses of corticosteroids, most often occurring in patients with disorders of neuromuscular transmission (eg, myasthenia gravis), or in patients receiving concomitant therapy with neuromuscular blocking drugs (eg, pancuronium). This acute myopathy is generalized, may involve ocular and respiratory muscles, and may result in quadriparesis. Elevation of creatinine kinase may occur. Clinical improvement or recovery after stopping corticosteroids may require weeks to years.

Psychic derangements may appear when corticosteroids are used, ranging from euphoria, insomnia, mood swings, personality changes, and severe depression to frank psychotic manifestations. Also, existing emotional instability or psychotic tendencies may be aggravated by corticosteroids.

Information for Patients

Patients should be warned not to discontinue the use of corticosteroids abruptly or without medical supervision, to advise any medical attendants that they are taking corticosteroids and to seek medical advice at once should they develop fever or other signs of infection.

Persons who are on corticosteroids should be warned to avoid exposure to chickenpox or measles. Patients should also be advised that if they are exposed, medical advice should be sought without delay.

Drug Interactions

Aminoglutethimide

Aminoglutethimide may lead to a loss of corticosteroid-induced adrenal suppression.

Amphotericin B Injection and Potassium-Depleting Agents

When corticosteroids are administered concomitantly with potassium-depleting agents (ie, amphotericin B, diuretics), patients should be observed closely for development of hypokalemia. There have been cases reported in which concomitant use of amphotericin B and hydrocortisone was followed by cardiac enlargement and congestive heart failure.

Antibiotics

Macrolide antibiotics have been reported to cause a significant decrease in corticosteroid clearance.

Anticholinesterases

Concomitant use of anticholinesterase agents and corticosteroids may produce severe weakness in patients with myasthenia gravis. If possible, anticholinesterase agents should be withdrawn at least 24 hours before initiating corticosteroid therapy.

Anticoagulants, Oral

Coadministration of corticosteroids and warfarin usually results in inhibition of response to warfarin, although there have been some conflicting reports. Therefore, coagulation indices should be monitored frequently to maintain the desired anticoagulant effect.

Antidiabetics

Because corticosteroids may increase blood glucose concentrations, dosage adjustments of antidiabetic agents may be required.

Antitubercular Drugs

Serum concentrations of isoniazid may be decreased.

Cholestyramine

Cholestyramine may increase the clearance of corticosteroids.

Cyclosporine

Increased activity of both cyclosporine and corticosteroids may occur when the two are used concurrently. Convulsions have been reported with this concurrent use.

Digitalis Glycosides

Patients on digitalis glycosides may be at increased risk of arrhythmias due to hypokalemia.

Estrogens, Including Oral Contraceptives

Estrogens may decrease the hepatic metabolism of certain corticosteroids, thereby increasing their effect.

Hepatic Enzyme Inducers (eg, barbiturates, phenytoin, carbamazepine, rifampin)

Drugs which induce hepatic microsomal drug-metabolizing enzyme activity may enhance the metabolism of corticosteroids and require that the dosage of the corticosteroid be increased.

Interactions with Strong CYP3A4 Inhibitors

Corticosteroids (including betamethasone) are metabolized by CYP3A4.

Ketoconazole has been reported to decrease the metabolism of certain corticosteroids by up to 60%, leading to an increased risk of corticosteroid side effects.

Coadministration with other strong CYP3A4 inhibitors (eg, itraconazole, clarithromycin, ritonavir, cobicistat-containing products) may lead to increased exposures of corticosteroids and therefore the potential for increased risk of systemic corticosteroid side effects.

Consider the benefit of coadministration versus the potential risk of systemic corticosteroid effects, in which case patients should be monitored for systemic corticosteroid side effects.

Nonsteroidal Anti-inflammatory Agents (NSAIDS)

Concomitant use of aspirin (or other nonsteroidal anti-inflammatory agents) and corticosteroids increases the risk of gastrointestinal side effects. Aspirin should be used cautiously in conjunction with corticosteroids in hypoprothrombinemia. The clearance of salicylates may be increased with concurrent use of corticosteroids.

Skin Tests

Corticosteroids may suppress reactions to skin tests.

Vaccines

Patients on prolonged corticosteroid therapy may exhibit a diminished response to toxoids and live or inactivated vaccines due to inhibition of antibody response. Corticosteroids may also potentiate the replication of some organisms contained in live attenuated vaccines. Route administration of vaccines or toxoids should be deferred until corticosteroid therapy is discontinued if possible (see WARNINGS, Infections, Vaccinationsection).

Carcinogenesis, Mutagenesis, Impairment of Fertility

No adequate studies have been conducted in animals to determine whether corticosteroids have a potential for carcinogenesis or mutagenesis.

Steroids may increase or decrease motility and number of spermatozoa in some patients.

Pregnancy

Teratogenic Effects

Corticosteroids have been shown to be teratogenic in many species when given in doses equivalent to the human dose. Animal studies in which corticosteroids have been given to pregnant mice, rats, and rabbits have yielded an increased incidence of cleft palate in the offspring. There are no adequate and well-controlled studies in pregnant women. Corticosteroids should be used during pregnancy only if the potential benefit justifies the potential risk to the fetus. Infants born to mothers who have received corticosteroids during pregnancy should be carefully observed for signs of hypoadrenalism.

Nursing Mothers

Systemically administered corticosteroids appear in human milk and could suppress growth, interfere with endogenous corticosteroid production, or cause other untoward effects. Caution should be exercised when corticosteroids are administered to a nursing woman.

Pediatric Use

The efficacy and safety of corticosteroids in the pediatric population are based on the well-established course of effect of corticosteroids, which is similar in pediatric and adult populations. Published studies provide evidence of efficacy and safety in pediatric patients for the treatment of nephrotic syndrome (>2 years of age), and aggressive lymphomas and leukemias (>1 month of age). Other indications for pediatric use of corticosteroids, eg, severe asthma and wheezing, are based on adequate and well-controlled trials conducted in adults, on the premises that the course of the diseases and their pathophysiology are considered to be substantially similar in both populations.

The adverse effects of corticosteroids in pediatric patients are similar to those in adults (see ADVERSE REACTIONS). Like adults, pediatric patients should be carefully observed with frequent measurements of blood pressure, weight, height, intraocular pressure, and clinical evaluation for the presence of infection, psychosocial disturbances, thromboembolism, peptic ulcers, cataracts, and osteoporosis. Pediatric patients who are treated with corticosteroids by any route, including systemically administered corticosteroids, may experience a decrease in their growth velocity. This negative impact of corticosteroids on growth has been observed at low systemic doses and in the absence of laboratory evidence of HPA axis suppression (ie, cosyntropin stimulation and basal cortisol plasma levels). Growth velocity may therefore be a more sensitive indicator of systemic corticosteroid exposure in pediatric patients than some commonly used tests of HPA axis function. The linear growth of pediatric patients treated with corticosteroids should be monitored, and the potential growth effects of prolonged treatment should be weighed against clinical benefits obtained and the availability of treatment alternatives. In order to minimize the potential growth effects of corticosteroids, pediatric patients should be titrated to the lowest effective dose.

Neonatal hypoglycemia has been reported after antenatal administration, especially in preterm, low birth weight infants, and when betamethasone is administered close to the time of delivery.

Geriatric Use

No overall differences in safety or effectiveness were observed between elderly subjects and younger subjects, and other reported clinical experience has not identified differences in responses between the elderly and young patients, but greater sensitivity of some older individuals cannot be ruled out.

ADVERSE REACTIONS (listed alphabetically, under each subsection)

Allergic Reactions

Anaphylactoid reaction, anaphylaxis, angioedema.

Cardiovascular

Bradycardia, cardiac arrest, cardiac arrhythmias, cardiac enlargement, circulatory collapse, congestive heart failure, fat embolism, hypertension, hypertrophic cardiomyopathy in premature infants, myocardial rupture following recent myocardial infarction (see WARNINGS), pulmonary edema, syncope, tachycardia, thromboembolism, thrombophlebitis, vasculitis.

Dermatologic

Acne, allergic dermatitis, cutaneous and subcutaneous atrophy, dry scaly skin, ecchymoses and petechiae, edema, erythema, hyperpigmentation, hypopigmentation, impaired wound healing, increased sweating, rash, sterile abscess, striae, suppressed reactions to skin tests, thin fragile skin, thinning scalp hair, urticaria.

Endocrine

Decreased carbohydrate and glucose tolerance, development of cushingoid state, glucosuria, hirsutism, hypertrichosis, increased requirements for insulin or oral hypoglycemic adrenocortical and pituitary unresponsiveness (particularly in times of stress, as in trauma, surgery, or illness), suppression of growth in pediatric patients.

Fluid and Electrolyte Disturbances

Congestive heart failure in susceptible patients, fluid retention, hypokalemic alkalosis, potassium loss, sodium retention.

Gastrointestinal

Abdominal distention, bowel/bladder dysfunction (after intrathecal administration), elevation in serum liver enzyme levels (usually reversible upon discontinuation), hepatomegaly, increased appetite, nausea, pancreatitis, peptic ulcer with possible perforation and hemorrhage, perforation of the small and large intestine (particularly in patients with inflammatory bowel disease), ulcerative esophagitis.

Metabolic

Negative nitrogen balance due to protein catabolism.

Musculoskeletal

Aseptic necrosis of femoral and humeral heads, calcinosis (following intra-articular or intralesional use), Charcot-like arthropathy, loss of muscle mass, muscle weakness, osteoporosis, pathologic fracture of long bones, postinjection flare (following intra-articular use), steroid myopathy, tendon rupture, vertebral compression fractures.

Neurologic/Psychiatric

Convulsions, depression, emotional instability, euphoria, headache, increased intracranial pressure with papilledema (pseudotumor cerebri) usually following discontinuation of treatment, insomnia, mood swings, neuritis, neuropathy, paresthesia, personality changes, psychic disorders, vertigo. Arachnoiditis, meningitis, paraparesis/paraplegia, and sensory disturbances have occurred after intrathecal administration (see WARNINGS, Neurologicsection).

Ophthalmic

Exophthalmos, glaucoma, increased intraocular pressure, posterior subcapsular cataracts, rare instances of blindness associated with periocular injections, vision blurred.

Other

Abnormal fat deposits, decreased resistance to infection, hiccups, increased or decreased motility and number of spermatozoa, malaise, moon face, weight gain.

OVERDOSAGE

Treatment of acute overdose is by supportive and symptomatic therapy. For chronic overdosage in the face of severe disease requiring continuous steroid therapy, the dosage of the corticosteroid may be reduced only temporarily, or alternate day treatment may be introduced.

DOSAGE AND ADMINISTRATION

Benzyl alcohol as a preservative has been associated with a fatal "Gasping Syndrome" in premature infants and infants of low birth weight. Solutions used for further dilution of this product should be preservative-free when used in the neonate, especially the premature infant. The initial dosage of parenterally administered CELESTONE®SOLUSPAN®Injectable Suspension may vary from 0.25 to 9.0 mg per day depending on the specific disease entity being treated. However, in certain overwhelming, acute, life-threatening situations, administrations in dosages exceeding the usual dosages may be justified and may be in multiples of the oral dosages.

It Should Be Emphasized That Dosage Requirements Are Variable and Must Be Individualized on the Basis of the Disease Under Treatment and the Response of the Patient.After a favorable response is noted, the proper maintenance dosage should be determined by decreasing the initial drug dosage in small decrements at appropriate time intervals until the lowest dosage which will maintain an adequate clinical response is reached. Situations which may make dosage adjustments necessary are changes in clinical status secondary to remissions or exacerbations in the disease process, the patient's individual drug responsiveness, and the effect of patient exposure to stressful situations not directly related to the disease entity under treatment. In this latter situation it may be necessary to increase the dosage of the corticosteroid for a period of time consistent with the patient's condition. If after long-term therapy the drug is to be stopped, it is recommended that it be withdrawn gradually rather than abruptly.

In the treatment of acute exacerbations of multiple sclerosis, daily doses of 30 mg of betamethasone for a week followed by 12 mg every other day for 1 month are recommended (see PRECAUTIONS, Neuro-psychiatricsection).

In pediatric patients, the initial dose of betamethasone may vary depending on the specific disease entity being treated. The range of initial doses is 0.02 to 0.3 mg/kg/day in three or four divided doses (0.6 to 9 mg/m^2bsa/day).

For the purpose of comparison, the following is the equivalent milligram dosage of the various glucocorticoids:

Cortisone, 25 | Triamcinolone, 4
Hydrocortisone, 20 | Paramethasone, 2
Prednisolone, 5 | Betamethasone, 0.75
Prednisone, 5 | Dexamethasone, 0.75
Methylprednisolone, 4

These dose relationships apply only to oral or intravenous administration of these compounds. When these substances or their derivatives are injected intramuscularly or into joint spaces, their relative properties may be greatly altered.

If coadministration of a local anesthetic is desired, CELESTONE SOLUSPAN Injectable Suspension may be mixed with 1% or 2% lidocaine hydrochloride, using the formulations which do not contain parabens. Similar local anesthetics may also be used. Diluents containing methylparaben, propylparaben, phenol, etc., should be avoided, since these compounds may cause flocculation of the steroid. The required dose of CELESTONE SOLUSPAN Injectable Suspension is first withdrawn from the vial into the syringe. The local anesthetic is then drawn in, and the syringe shaken briefly. Do not inject local anesthetics into the vial of CELESTONE SOLUSPAN Injectable Suspension.

Bursitis, Tenosynovitis, Peritendinitis

In acute subdeltoid, subacromial, olecranon, and prepatellar bursitis, one intrabursal injection of 1.0 mL CELESTONE SOLUSPAN Injectable Suspension can relieve pain and restore full range of movement. Several intrabursal injections of corticosteroids are usually required in recurrent acute bursitis and in acute exacerbations of chronic bursitis. Partial relief of pain and some increase in mobility can be expected in both conditions after one or two injections. Chronic bursitis may be treated with reduced dosage once the acute condition is controlled. In tenosynovitis and tendinitis, three or four local injections at intervals of 1 to 2 weeks between injections are given in most cases. Injections should be made into the affected tendon sheaths rather than into the tendons themselves. In ganglions of joint capsules and tendon sheaths, injection of 0.5 mL directly into the ganglion cysts has produced marked reduction in the size of the lesions.

Rheumatoid Arthritis and Osteoarthritis

Following intra-articular administration of 0.5 to 2.0 mL of CELESTONE SOLUSPAN Injectable Suspension, relief of pain, soreness, and stiffness may be experienced. Duration of relief varies widely in both diseases. Intra-articular Injection of CELESTONE SOLUSPAN Injectable Suspension is well tolerated in joints and periarticular tissues. There is virtually no pain on injection, and the "secondary flare" that sometimes occurs a few hours after intra-articular injection of corticosteroids has not been reported with CELESTONE SOLUSPAN Injectable Suspension. Using sterile technique, a 20- to 24-gauge needle on an empty syringe is inserted into the synovial cavity and a few drops of synovial fluid are withdrawn to confirm that the needle is in the joint. The aspirating syringe is replaced by a syringe containing CELESTONE SOLUSPAN Injectable Suspension and injection is then made into the joint.

Recommended Doses for Intra-articular Injection
Size of joint | Location | Dose (mL)
Very large | Hip | 1.0-2.0
Large | Knee, ankle, shoulder | 1.0
Medium | Elbow, wrist | 0.5-1.0
Small (metacarpophalangeal, interphalangeal) (sternoclavicular) | Hand, chest | 0.25-0.5

A portion of the administered dose of CELESTONE SOLUSPAN Injectable Suspension is absorbed systemically following intra-articular injection. In patients being treated concomitantly with oral or parenteral corticosteroids, especially those receiving large doses, the systemic absorption of the drug should be considered in determining intra-articular dosage.

Dermatologic Conditions

In intralesional treatment, 0.2 mL/cm^2of CELESTONE SOLUSPAN Injectable Suspension is injected intradermally (not subcutaneously) using a tuberculin syringe with a 25-gauge, ½-inch needle. Care should be taken to deposit a uniform depot of medication intradermally. A total of no more than 1.0 mL at weekly intervals is recommended.

Disorders of the Foot

A tuberculin syringe with a 25-gauge, ¾-inch needle is suitable for most injections into the foot. The following doses are recommended at intervals of 3 days to a week.

Diagnosis | CELESTONE SOLUSPAN Injectable Suspension Dose (mL)
Bursitis under heloma durum or heloma molle | 0.25-0.5
under calcaneal spur | 0.5
over hallux rigidus or digiti quinti varus | 0.5
Tenosynovitis, periostitis of cuboid | 0.5
Acute gouty arthritis | 0.5-1.0

HOW SUPPLIED

CELESTONE®SOLUSPAN®Injectable Suspension is supplied as follows:

NDC 85766-070-05 [relabeled from NDC 78206-118-01]:

CELESTONE SOLUSPAN Injectable Suspension, 5-mL multiple-dose vial; box of one. Inactive ingredients per mL: 8.9 mg dibasic sodium phosphate dihydrate; 3.8 mg monobasic sodium phosphate dihydrate; 0.1 mg edetate disodium; and 0.2 mg benzalkonium chloride as preservative.

SHAKE WELL BEFORE USING.

STORAGE AND HANDLING

Store at 25°C (77°F); excursions permitted to 15°C-30°C (59°-86°F) [see USP Controlled Room Temperature].

Protect from light.

Rx only

Distributed by:

Sportpharm

2237 N Commerce Parkway,

STE 1, Weston, Florida-33326

Relabeled by:

Enovachem PHARMACEUTICALS

Torrance, CA 90501